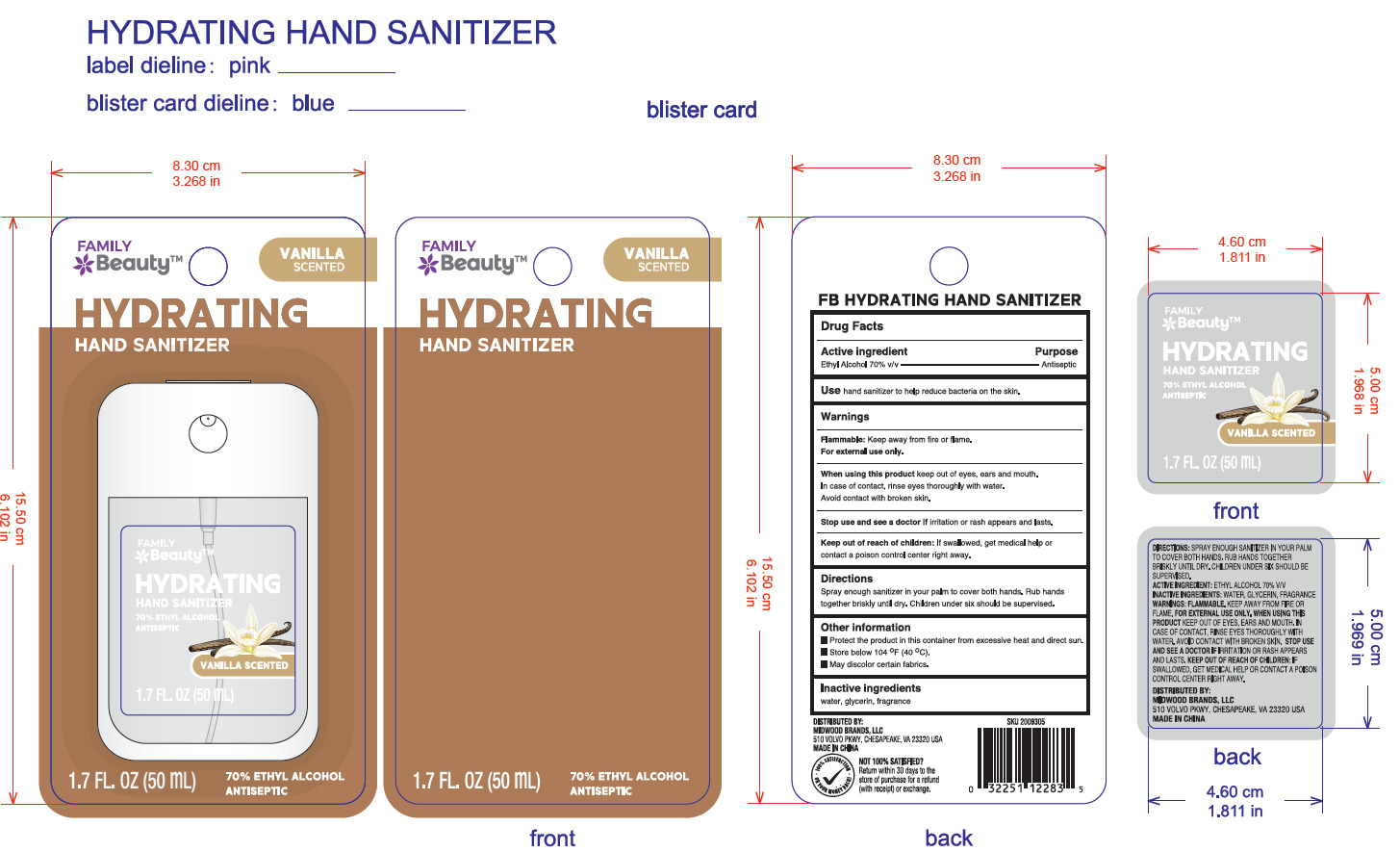 DRUG LABEL: FB HYDRATING HAND SANITIZER
NDC: 55319-778 | Form: GEL
Manufacturer: FAMILY DOLLAR SERVICES, LLC
Category: otc | Type: HUMAN OTC DRUG LABEL
Date: 20251030

ACTIVE INGREDIENTS: ALCOHOL 70 g/100 mL
INACTIVE INGREDIENTS: WATER; GLYCERIN

55319-778

Active Ingredient(s)

Ethyl Alcohol 70%

Purpose

Antiseptic

Use

Use hand sanitizer to help reduce bacteria on the skin

Warnings

Flammable: Keep away from fire or flame.

For external use only.

Do not use

Do not using children less than 2 months of age on open skin wounds.

When using this product keep out of eyes, ears and mouth. In case of contact, rinse eyes thoroughly with water.
Avoid contact with broken skin.

Stop use and see a doctor if irritation or rash appears and lasts.

Keep out of reach of children: If swallowed, get medical help or contact a poison control center right away.

Directions

Spray enough sanitizer in your palm to cover both hands. Rub hands together briskly until dry. Children under six should be supervised.

Other information

① Protect the product in this container from excessive heat and direct sun.

② Store below 104° F (40°C).

③ May discolor certain fabrics.

Inactive ingredients

water, glycerin, fragrance